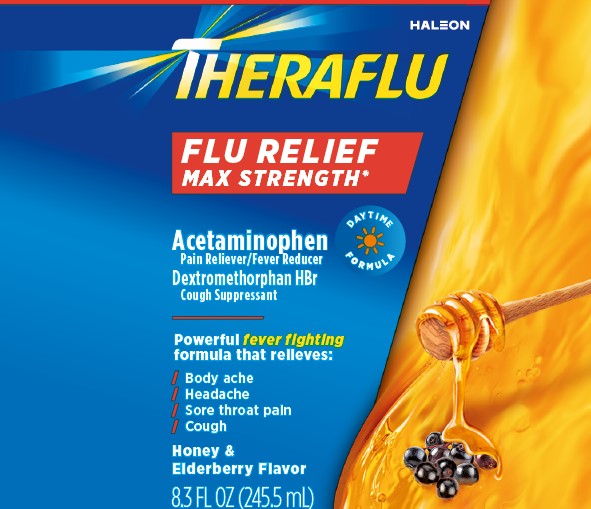 DRUG LABEL: Theraflu Flu Relief Max Strength
NDC: 0067-8204 | Form: SYRUP
Manufacturer: Haleon US Holdings LLC
Category: otc | Type: HUMAN OTC DRUG LABEL
Date: 20260107

ACTIVE INGREDIENTS: ACETAMINOPHEN 1000 mg/30 mL; DEXTROMETHORPHAN HYDROBROMIDE 30 mg/30 mL
INACTIVE INGREDIENTS: CARBOXYMETHYLCELLULOSE SODIUM, UNSPECIFIED; GLYCERIN; HONEY; POLYETHYLENE GLYCOL, UNSPECIFIED; PROPYLENE GLYCOL; WATER; SODIUM BENZOATE; SODIUM CITRATE, UNSPECIFIED FORM; SODIUM GLUCONATE; SUCRALOSE; XANTHAN GUM; ZINC GLUCONATE

Drug Facts

Active ingredients (in each 30 mL)

Acetaminophen 1000 mg

Dextromethorphan HBr 30 mg

Purposes

Pain reliever/Fever reducer

Cough suppressant

Uses

- temporarily relieves these symptoms due to a common cold or flu:
  - headache
  - minor aches and pains
  - cough due to minor throat and bronchial irritation
  - minor sore throat pain
- temporarily reduces fever

Warnings

Liver warning: This product contains acetaminophen. Severe liver damage may occur if you take

- more than 4,000 mg of acetaminophen in 24 hours
- with other drugs containing acetaminophen
- 3 or more alcoholic drinks every day while using this product

Allergy alert: Acetaminophen may cause severe skin reactions. Symptoms may include:

- skin reddening
- blisters
- rash
If a skin reaction occurs, stop use and seek medical help right away.

Sore throat warning: If sore throat is severe, persists for more than 2 days, is accompanied or followed by fever, headache, rash, nausea, or vomiting consult a doctor promptly.

Do not use

- in a child under 12 years of age
- if you are allergic to acetaminophen
- with any other drug containing acetaminophen (prescription or nonprescription). If you are not sure whether a drug contains acetaminophen, ask a doctor or pharmacist.
- if you are now taking a prescription monoamine oxidase inhibitor (MAOI) (certain drugs for depression, psychiatric, or emotional conditions, or Parkinson’s disease), or for 2 weeks after stopping the MAOI drug. If you do not know if your prescription drug contains an MAOI, ask a doctor or pharmacist before taking this product.

Ask a doctor before use if you have

- liver disease
- cough that occurs with too much phlegm (mucus)
- cough that lasts or is chronic such as occurs with smoking, asthma or emphysema

Ask a doctor or pharmacist before use if you are

- taking the blood thinning drug warfarin

Stop use and ask a doctor if

- pain or cough gets worse or lasts more than 7 days
- fever gets worse or lasts more than 3 days
- redness or swelling is present
- new symptoms occur
- cough comes back or occurs with rash or headache that lasts
These could be signs of a serious condition.

If pregnant or breast-feeding,

ask a health professional before use.

Keep out of reach of children.

In case of overdose, get medical help or contact a Poison Control Center right away. Prompt medical attention is critical for adults as well as for children even if you do not notice any signs or symptoms.

Directions

- do not use more than directed
- measure the dose correctly using the enclosed dosing cup
- adults and children 12 years of age and over: take every 6 hours in dosing cup provided, while symptoms persist
- do not take more than 3 doses (90 mL) in 24 hours unless directed by a doctor
- children under 12 years of age: do not use

Age | Dose
adults and children 12 years of age and over | 30 mL
children under 12 years of age | do not use

Other information

- each 30 mL contains: potassium 5 mg, sodium 34 mg
- store at controlled room temperature 20-25°C (68-77°F).

Inactive ingredients

anhydrous citric acid, carboxymethylcellulose sodium, glycerin, natural and artificial flavors, natural grade A honey, polyethylene glycol, propylene glycol, purified water, sodium benzoate, sodium citrate, sodium gluconate, sucralose, xanthan gum, zinc gluconate

Questions or comments?

1-855-328-5259

Additional Information

PEEL BACK HERE

DO NOT TAKE MORE THAN 3 DOSES IN TOTAL IN ANY 24 HOUR PERIOD. USE AS DIRECTED

DO NOT USE IF NECKBAND PRINTED WITH “SEALED FOR SAFETY” IS TORN OR MISSING.

*Maximum Strength per 6 hour dose.

PARENTS: Learn about teen medicine abuse

www.StopMedicineAbuse.org

Pat. Info www.productpats.com

Principal Display Panel

THERAFLU

FLU RELIEF

MAX STRENGTH*

Acetaminophen

Pain Reliever/Fever Reducer

Dextromethorphan HBr

Cough Suppressant

DAYTIME FORMULA

Powerful fever fighting formula that relieves:

/ Body ache

/ Headache

/ Sore throat pain

/ Cough

Honey & Elderberry Flavor

8.3 FL OZ (245.5mL)